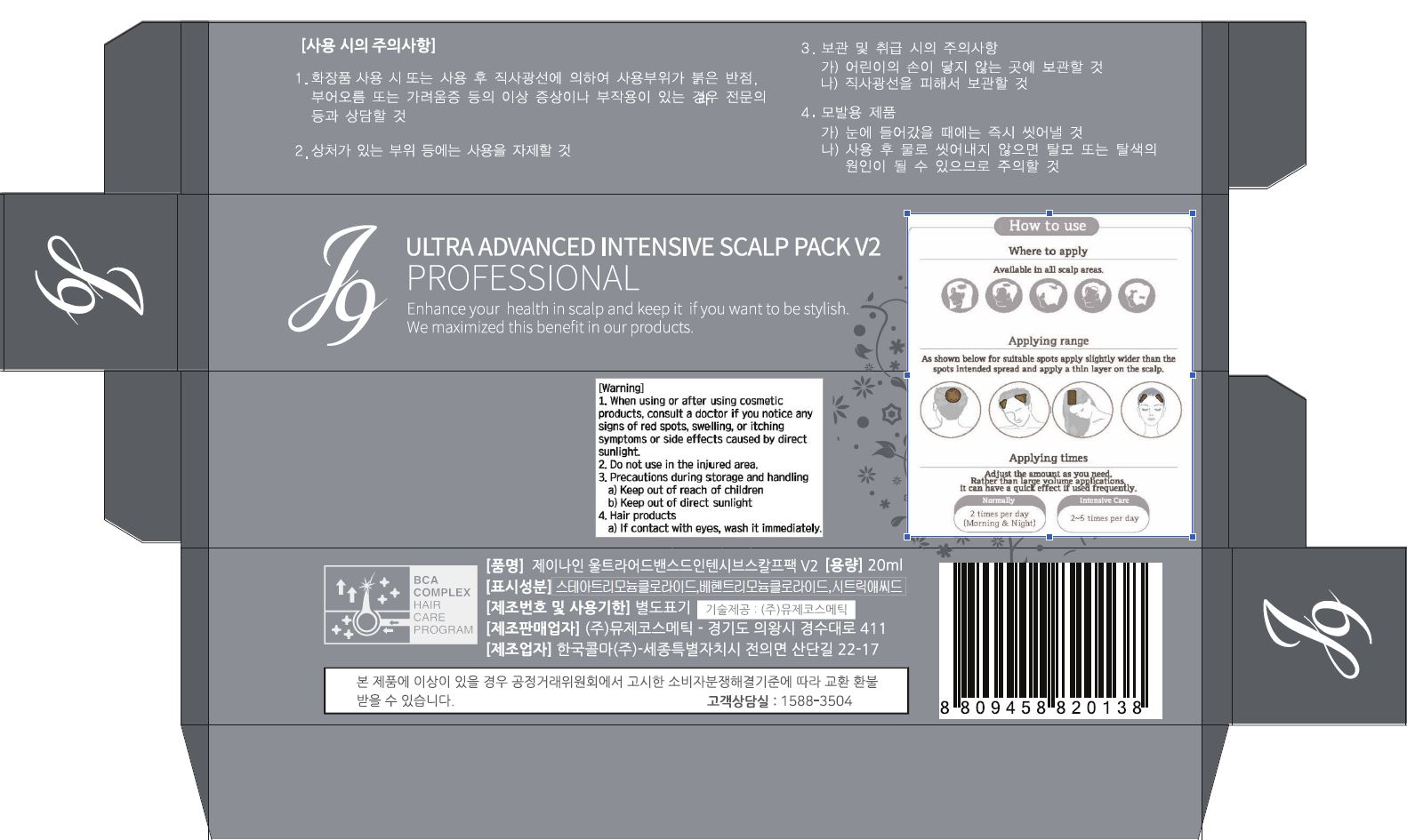 DRUG LABEL: J9 ULTRA ADVANCED INTENSIVE SCALP PACK V2
NDC: 70488-0011 | Form: CREAM
Manufacturer: MUSEE Cosmetic Co.,Ltd.
Category: otc | Type: HUMAN OTC DRUG LABEL
Date: 20190412

ACTIVE INGREDIENTS: DIMETHICONE 1 g/100 mL
INACTIVE INGREDIENTS: WATER; BENTONITE

Drug Facts

ACTIVE INGREDIENT

dimethicone

INACTIVE INGREDIENT

WATER
BENTONITE
CETEARYL ALCOHOL
BEHENYL ALCOHOL
PROPYLENE GLYCOL
STEARTRIMONIUM CHLORIDE
WATER
BEHENTRIMONIUM CHLORIDE
ISOPROPYL ALCOHOL
1,2-HEXANEDIOL
CYCLOPENTASILOXANE
FRAGRANCE
PEG-14M
PERSEA GRATISSIMA (AVOCADO) OIL
DISODIUM EDTA
SODIUM CITRATE
CITRIC ACID
PANTHENOL
WATER
BUTYLENE GLYCOL
CHITOSAN SUCCINAMIDE

PURPOSE

enhance you health in scalp and akeep it if you want to be stylish

keep out of reach of the children

INDICATIONS AND USAGE

Apply to the scalp and gently rub it to absorb it

WARNINGS

1. when using or after using comsetic products, consult a doctor if you notice any signs of red spots, swelling, or itching symptoms or side effects caused by direct sunlight

2. do not use in the injured area

3. precautions during storage and handling

a) keep out of reach of children

b) keep out of direct sunlight

4. if contact with eyes, wash it immediately

DOSAGE AND ADMINISTRATION

for topical use only